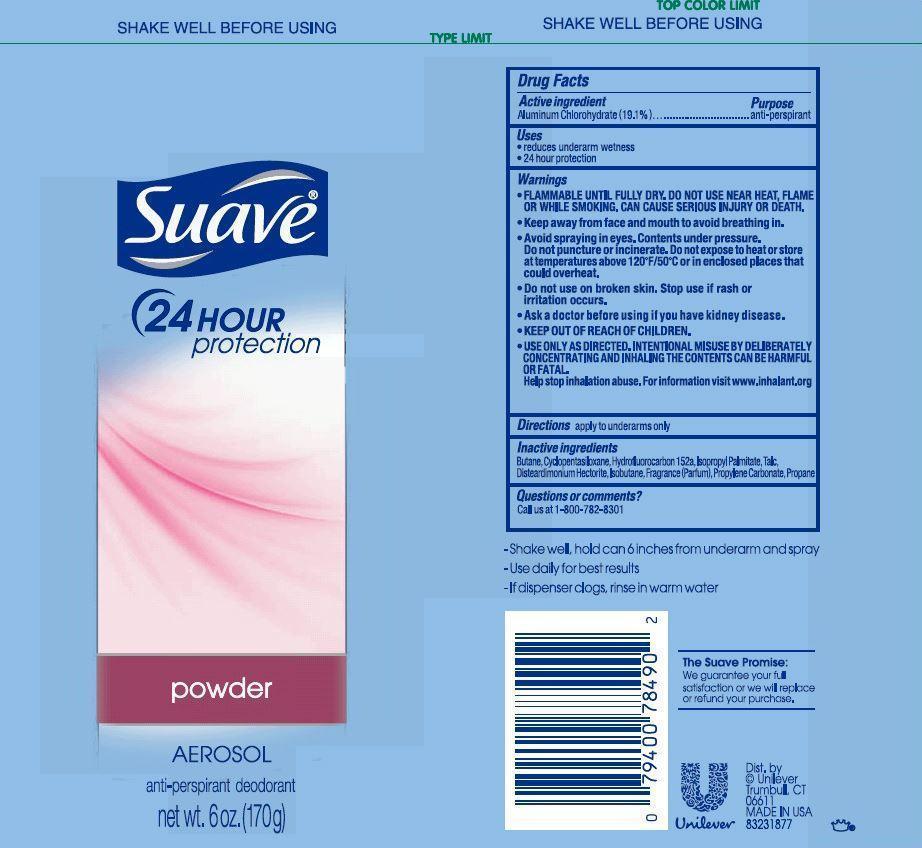 DRUG LABEL: Suave
NDC: 64942-1427 | Form: AEROSOL, SPRAY
Manufacturer: Conopco Inc. d/b/a Unilever
Category: otc | Type: HUMAN OTC DRUG LABEL
Date: 20221207

ACTIVE INGREDIENTS: ALUMINUM CHLOROHYDRATE 19.1 g/100 g
INACTIVE INGREDIENTS: BUTANE; 1,1-DIFLUOROETHANE; CYCLOMETHICONE 5; ISOBUTANE; ISOPROPYL PALMITATE; TALC; DISTEARDIMONIUM HECTORITE; PROPANE

Suave 24 hour Powder Aerosol Antiperspirant

Active Ingredient:

Aluminum Chlorohydrate (19.1%)

Purpose:

anti-perspirant

Uses

· reduces underarm wetness

· 24 hour protection

WARNINGS:

• FLAMMABLE UNTIL FULLY DRY. DO NOT USE NEAR HEAT, FLAME OR WHILE SMOKING. CAN CAUSE SERIOUS INJURY OR DEATH.
• Keep away from face and mouth to avoid breathing in.
• Avoid spraying in eyes. Contents under pressure. Do not puncture or incinerate. Do not expose to heat or store at temperatures above 120 degrees F/50 degrees C or in enclosed places that could overheat.
• Do not use on broken skin. Stop use if rash or irritation occurs.
• Ask a doctor before using if you have kidney disease.
• USE ONLY AS DIRECTED. INTENTIONAL MISUSE BY DELIBERATELY CONCENTRATING AND INHALING THE CONTENTS CAN BE HARMFUL OR FATAL. Help stop inhalation abuse. For information visit www.inhalant.org

• KEEP OUT OF REACH OF CHILDREN

Directions

apply to underarms only

Inactive Ingredients

Butane, Cyclopentasiloxane, Hydrofluorocarbon 152a, Isopropyl Palmitate, Talc, Disteardimonium Hectorite, Isobutane, Propylene Carbonate, Fragrance (Parfum), Propane

Questions or comments?

Call us at 1-800-782-8301

INSTRUCTIONS FOR USE

- Shake well, hold can about six inches from underarm and spray

- Use daily for best results

- If dispenser clogs, rinse in warm water